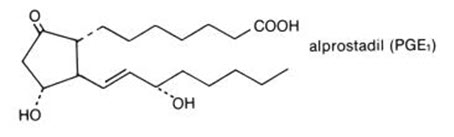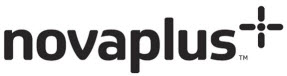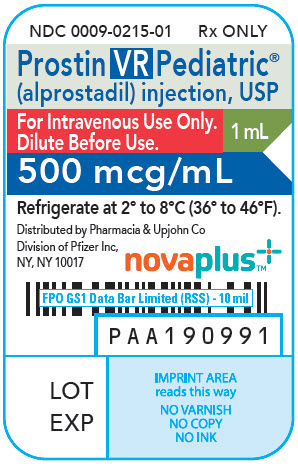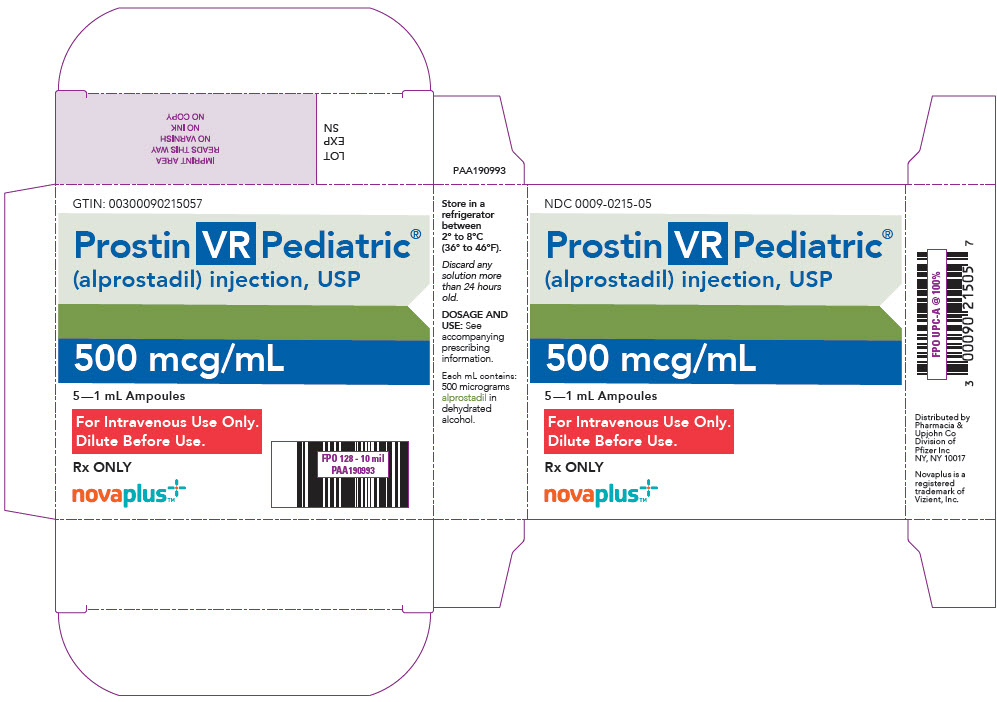 DRUG LABEL: PROSTIN
NDC: 0009-0215 | Form: INJECTION, SOLUTION
Manufacturer: Pharmacia & Upjohn Company LLC
Category: prescription | Type: HUMAN PRESCRIPTION DRUG LABEL
Date: 20260219

ACTIVE INGREDIENTS: ALPROSTADIL 500 ug/1 mL
INACTIVE INGREDIENTS: ALCOHOL

Prostin VR Pediatric®
alprostadil injection, USP

500 micrograms per mL

WARNING

Apnea is experienced by about 10 to 12% of neonates with congenital heart defects treated with PROSTIN VR PEDIATRIC Sterile Solution. Apnea is most often seen in neonates weighing less than 2 kg at birth and usually appears during the first hour of drug infusion. Therefore, respiratory status should be monitored throughout treatment, and PROSTIN VR PEDIATRIC should be used where ventilatory assistance is immediately available.

DESCRIPTION

PROSTIN VR PEDIATRIC Sterile Solution for intravascular infusion contains 500 micrograms alprostadil, more commonly known as prostaglandin E1, in 1.0 mL dehydrated alcohol.

The chemical name for alprostadil is (11α,13E,15S)-11,15 dihydroxy-9-oxo-prost-13-en-1-oic acid, and the molecular weight is 354.49.

Alprostadil is a white to off-white crystalline powder with a melting point between 110° and 116°C. Its solubility at 35°C is 8000 micrograms per 100 mL double distilled water.

Structural Formula

CLINICAL PHARMACOLOGY

Alprostadil (prostaglandin E1) is one of a family of naturally occurring acidic lipids with various pharmacologic effects. Vasodilation, inhibition of platelet aggregation, and stimulation of intestinal and uterine smooth muscle are among the most notable of these effects. Intravenous doses of 1 to 10 micrograms of alprostadil per kilogram of body weight lower the blood pressure in mammals by decreasing peripheral resistance. Reflex increases in cardiac output and rate accompany the reduction in blood pressure.

Smooth muscle of the ductus arteriosus is especially sensitive to alprostadil, and strips of lamb ductus markedly relax in the presence of the drug. In addition, administration of alprostadil reopened the closing ductus of new-born rats, rabbits, and lambs. These observations led to the investigation of alprostadil in infants who had congenital defects which restricted the pulmonary or systemic blood flow and who depended on a patent ductus arteriosus for adequate blood oxygenation and lower body perfusion.

In infants with restricted pulmonary blood flow, about 50% responded to alprostadil infusion with at least a 10 torr increase in blood pO2 (mean increase about 14 torr and mean increase in oxygen saturation about 23%). In general, patients who responded best had low pretreatment blood pO2 and were 4 days old or less.

In infants with restricted systemic blood flow, alprostadil often increased pH in those having acidosis, increased systemic blood pressure, and decreased the ratio of pulmonary artery pressure to aortic pressure.

Alprostadil must be infused continuously because it is very rapidly metabolized. As much as 80% of the circulating alprostadil may be metabolized in one pass through the lungs, primarily by β- and ω- oxidation. The metabolites are excreted primarily by the kidney, and excretion is essentially complete within 24 hours after administration. No unchanged alprostadil has been found in the urine, and there is no evidence of tissue retention of alprostadil or its metabolites.

INDICATIONS AND USAGE

PROSTIN VR PEDIATRIC Sterile Solution is indicated for palliative, not definitive, therapy to temporarily maintain the patency of the ductus arteriosus until corrective or palliative surgery can be performed in neonates who have congenital heart defects and who depend upon the patent ductus for survival. Such congenital heart defects include pulmonary atresia, pulmonary stenosis, tricuspid atresia, tetralogy of Fallot, interruption of the aortic arch, coarctation of the aorta, or transposition of the great vessels with or without other defects.

In infants with restricted pulmonary blood flow, the increase in blood oxygenation is inversely proportional to pretreatment pO2 values; that is, patients with low pO2 values respond best, and patients with pO2 values of 40 torr or more usually have little response.

PROSTIN VR PEDIATRIC should be administered only by trained personnel in facilities that provide pediatric intensive care.

CONTRAINDICATIONS

None.

WARNINGS

See WARNING box.

NOTE: PROSTIN VR PEDIATRIC Sterile Solution must be diluted before it is administered. See dilution instructions in DOSAGE AND ADMINISTRATION section.

The administration of PROSTIN VR PEDIATRIC to neonates may result in gastric outlet obstruction secondary to antral hyperplasia. This effect appears to be related to duration of therapy and cumulative dose of the drug. Neonates receiving PROSTIN VR PEDIATRIC at recommended doses for more than 120 hours should be closely monitored for evidence of antral hyperplasia and gastric outlet obstruction.

PROSTIN VR PEDIATRIC should be infused for the shortest time and at the lowest dose that will produce the desired effects. The risks of long-term infusion of PROSTIN VR PEDIATRIC should be weighed against the possible benefits that critically ill infants may derive from its administration.

PRECAUTIONS

General Precautions

Cortical proliferation of the long bones, first observed in dogs, has also been observed in infants during long-term infusions of alprostadil. The cortical proliferation in infants regressed after withdrawal of the drug.

In infants treated with PROSTIN VR PEDIATRIC at the usual doses for 10 hours to 12 days and who died of causes unrelated to ductus structural weakness, tissue sections of the ductus and pulmonary arteries have shown intimal lacerations, a decrease in medial muscularity and disruption of the medial and internal elastic lamina. Localized and aneurysmal dilatations and vessel wall edema also were seen compared to a series of pathological specimens from infants not treated with PROSTIN VR PEDIATRIC. The incidence of such structural alterations has not been defined.

Because alprostadil inhibits platelet aggregation, use PROSTIN VR PEDIATRIC cautiously in neonates with bleeding tendencies.

PROSTIN VR PEDIATRIC should not be used in neonates with respiratory distress syndrome. A differential diagnosis should be made between respiratory distress syndrome (hyaline membrane disease) and cyanotic heart disease (restricted pulmonary blood flow). If full diagnostic facilities are not immediately available, cyanosis (pO2 less than 40 torr) and restricted pulmonary blood flow apparent on an X-ray are appropriate indicators of congenital heart defects.

Necessary Monitoring

In all neonates, arterial pressure should be monitored intermittently by umbilical artery catheter, auscultation, or with a Doppler transducer. Should arterial pressure fall significantly, decrease the rate of infusion immediately.

In infants with restricted pulmonary blood flow, measure efficacy of PROSTIN VR PEDIATRIC by monitoring improvement in blood oxygenation. In infants with restricted systemic blood flow, measure efficacy by monitoring improvement of systemic blood pressure and blood pH.

PROSTIN VR PEDIATRIC contains ethanol (79% w/v). Ethanol may cause CNS depressant effects such as somnolence and may alter the effects of other medicines. Co‑administration with medicines containing e.g. propylene glycol or ethanol may lead to accumulation of ethanol and induce adverse effects, particularly in young children with low or immature metabolic capacity.

Drug Interactions

No drug interactions have been reported between PROSTIN VR PEDIATRIC and the therapy standard in neonates with restricted pulmonary or systemic blood flow. Standard therapy includes antibiotics, such as penicillin and gentamicin; vasopressors, such as dopamine and isoproterenol; cardiac glycosides; and diuretics, such as furosemide.

Carcinogenesis, Mutagenesis, and Impairment of Fertility

Long-term carcinogenicity studies and fertility studies have not been done. The Ames and Alkaline Elution assays reveal no potential for mutagenesis.

ADVERSE REACTIONS

Central Nervous System

Apnea has been reported in about 12% of the neonates treated. (See WARNING box.) Other common adverse reactions reported have been fever in about 14% of the patients treated and seizures in about 4%. The following reactions have been reported in less than 1% of the patients: cerebral bleeding, hyperextension of the neck, hyperirritability, hypothermia, jitteriness, lethargy, and stiffness.

Cardiovascular System

The most common adverse reactions reported have been flushing in about 10% of patients (more common after intraarterial dosing), bradycardia in about 7%, hypotension in about 4%, tachycardia in about 3%, cardiac arrest in about 1%, and edema in about 1%. The following reactions have been reported in less than 1% of the patients: congestive heart failure, hyperemia, second degree heart block, shock, spasm of the right ventricle infundibulum, supraventricular tachycardia, and ventricular fibrillation.

Respiratory System

The following reactions have been reported in less than 1% of the patients: bradypnea, bronchial wheezing, hypercapnia, respiratory depression, respiratory distress, and tachypnea.

Gastrointestinal System

See WARNINGS

The most common adverse reaction reported has been diarrhea in about 2% of the patients. The following reactions have been reported in less than 1% of the patients: gastric regurgitation, and hyperbilirubinemia.

Hematologic System

The most common hematologic event reported has been disseminated intravascular coagulation in about 1% of the patients. The following events have been reported in less than 1% of the patients: anemia, bleeding, and thrombocytopenia.

Excretory System

Anuria and hematuria have been reported in less than 1% of the patients.

Skeletal System

Cortical proliferation of the long bones has been reported. See PRECAUTIONS.

Miscellaneous

Sepsis has been reported in about 2% of the patients. Peritonitis has been reported in less than 1% of the patients. Hypokalemia has been reported in about 1%, and hypoglycemia and hyperkalemia have been reported in less than 1% of the patients.

OVERDOSAGE

Apnea, bradycardia, pyrexia, hypotension, and flushing may be signs of drug overdosage. If apnea or bradycardia occurs, discontinue the infusion, and provide appropriate medical treatment. Caution should be used in restarting the infusion. If pyrexia or hypotension occurs, reduce the infusion rate until these symptoms subside. Flushing is usually a result of incorrect intraarterial catheter placement, and the catheter should be repositioned.

DOSAGE AND ADMINISTRATION

The preferred route of administration for PROSTIN VR PEDIATRIC Sterile Solution is continuous intravenous infusion into a large vein. Alternatively, PROSTIN VR PEDIATRIC may be administered through an umbilical artery catheter placed at the ductal opening. Increases in blood pO2 (torr) have been the same in neonates who received the drug by either route of administration.

Begin infusion with 0.05 to 0.1 micrograms alprostadil per kilogram of body weight per minute. A starting dose of 0.1 micrograms per kilogram of body weight per minute is the recommended starting dose based on clinical studies; however, adequate clinical response has been reported using a starting dose of 0.05 micrograms per kilogram of body weight per minute. After a therapeutic response is achieved (increased pO2 in infants with restricted pulmonary blood flow or increased systemic blood pressure and blood pH in infants with restricted systemic blood flow), reduce the infusion rate to provide the lowest possible dosage that maintains the response. This may be accomplished by reducing the dosage from 0.1 to 0.05 to 0.025 to 0.01 micrograms per kilogram of body weight per minute. If response to 0.05 micrograms per kilogram of body weight per minute is inadequate, dosage can be increased up to 0.4 micrograms per kilogram of body weight per minute although, in general, higher infusion rates do not produce greater effects.

Dilution Instructions

To prepare infusion solutions, dilute 1 mL of PROSTIN VR PEDIATRIC Sterile Solution with Sodium Chloride Injection USP or Dextrose Injection USP. Undiluted PROSTIN VR PEDIATRIC Sterile Solution may interact with the plastic sidewalls of volumetric infusion chambers causing a change in the appearance of the chamber and creating a hazy solution. Should this occur, the solution and the volumetric infusion chamber should be replaced.

When using a volumetric infusion chamber, the appropriate amount of intravenous infusion solution should be added to the chamber first. The undiluted PROSTIN VR PEDIATRIC Sterile Solution should then be added to the intravenous infusion solution, avoiding direct contact of the undiluted solution with the walls of the volumetric infusion chamber.

Dilute to volumes appropriate for the pump delivery system available. Prepare fresh infusion solutions every 24 hours. Discard any solution more than 24 hours old.

Sample Dilutions and Infusion Rates to Provide a Dosage of 0.1 Micrograms per Kilogram of Body Weight per Minute
Add 1 ampoule (500 micrograms) alprostadil to: | Approximate Concentration of resulting solution (micrograms/mL) | Infusion rate (mL/min per kg of body weight)
250 mL | 2 | 0.05
100 mL | 5 | 0.02
50 mL | 10 | 0.01
25 mL | 20 | 0.005
Example: To provide 0.1 micrograms/kilogram of body weight per minute to an infant weighing 2.8 kilograms using a solution of 1 ampoule PROSTIN VR PEDIATRIC in 100 mL of saline or dextrose: INFUSION RATE = 0.02 mL/min per kg × 2.8 kg = 0.056 mL/min or 3.36 mL/hr.

HOW SUPPLIED

PROSTIN VR PEDIATRIC Sterile Solution is available in a package of 5 ×1 mL ampoules (NDC 0009-0215-05). Each mL contains 500 micrograms alprostadil in dehydrated alcohol.

STORAGE AND HANDLING

Store PROSTIN VR PEDIATRIC Sterile Solution in a refrigerator at 2° to 8°C (36° to 46°F).

Rx only

Distributed by
Pfizer Labs
Division of Pfizer Inc
New York, NY 10001

Novaplus is a registered trademark of Vizient, Inc.

LAB-1522-2.0
Revised December 2025

PRINCIPAL DISPLAY PANEL - 1 mL Ampoule Label

NDC 0009-0215-01
Rx ONLY

Prostin VR Pediatric®
(alprostadil) injection, USP

For Intravenous Use Only.
Dilute Before Use.

1 mL

500 mcg/mL

Refrigerate at 2° to 8°C (36° to 46°F).

Distributed by Pharmacia & Upjohn Co
Division of Pfizer Inc,
NY, NY 10017

novaplus™

PAA190991

LOT

EXP

PRINCIPAL DISPLAY PANEL - 1 mL Ampoule Package

NDC 0009-0215-05

Prostin VR Pediatric®
(alprostadil) injection, USP

500 mcg/mL

5—1 mL Ampoules

For Intravenous Use Only.
Dilute Before Use.

Rx ONLY

novaplus™